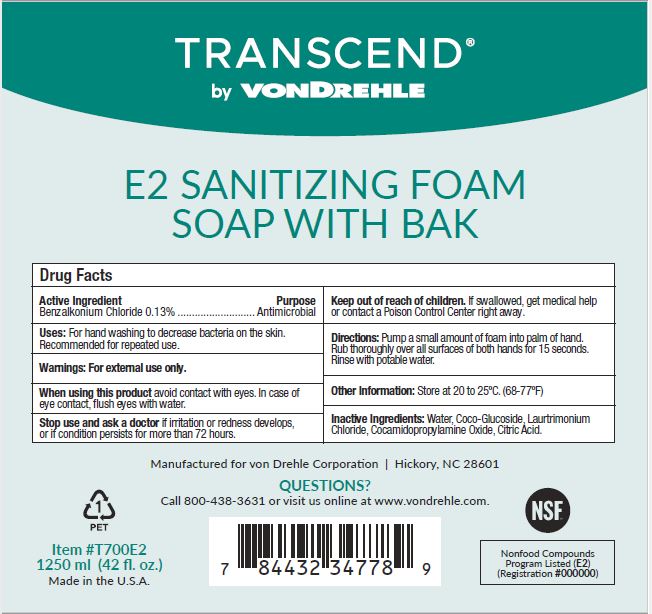 DRUG LABEL: Transcend E2 Sanitizing Foam
NDC: 81792-002 | Form: SOAP
Manufacturer: Von Drehle Corporation
Category: otc | Type: HUMAN OTC DRUG LABEL
Date: 20241125

ACTIVE INGREDIENTS: BENZALKONIUM CHLORIDE 1.3 mg/1 mL
INACTIVE INGREDIENTS: COCO GLUCOSIDE; LAURTRIMONIUM CHLORIDE; CITRIC ACID MONOHYDRATE; WATER; COCAMIDOPROPYLAMINE OXIDE

Von Drehle 81792-002

Active Ingredient

Benzalkonium Cloride 0.13%

Purpose

Antimicrobial

Uses:

For handwashing to decrease bacteria on the skin.

Recommended for repeated use.

Warnings:

For external use only.

When using this productavoid contact with eyes.

In case of eye contact, flush eyes with water.

Stop use and ask a doctorif irritation or redness develops, or if condition persists for more than 72 hours.

Keep out of reach of Children.

If swallowed, gert medical help or contact a Poison Control Center right away.

Directions:

Pump a small amount of foam into palm of hand.

Rub thoroughly over all surfaces of both hands for 15 seconds.

Rinse with potable water.

Other Information:

Store at 20 to 25C. (68-77F)

Inactive Ingredients:

Water, Coco-Glucoside, Laurtrimonium Chloride, Cocamidopropylamine Oxide, Citric Acid.

PACKAGE LABEL

TRANSCEND

by VONDREHLE

E2 SANITIZING FOAM

SOAP WITH BAK

Manufactured for von Drehle Corporation I Hickory, NC 28601

QUESTIONS?

Call 800-438-3631 or visit us online at www.vondrehle.com

NSF

Nonfood Compounds

Program Listed (E2)

(Registration #000000)

1

PET

Item #T700E2

1250 ml (42 fl. oz.

Made in the U.S. A.